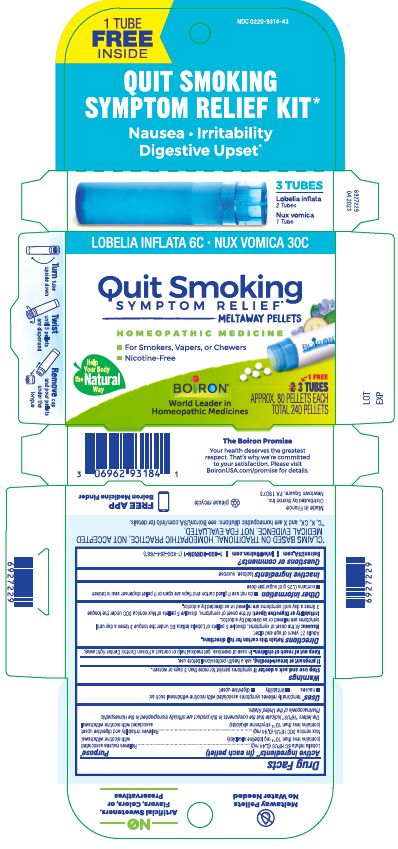 DRUG LABEL: Quit Smoking Symptom Relief
NDC: 0220-9318 | Form: PELLET
Manufacturer: Boiron
Category: homeopathic | Type: HUMAN OTC DRUG LABEL
Date: 20230705

ACTIVE INGREDIENTS: LOBELIA INFLATA 6 [hp_C]/1 1; STRYCHNOS NUX-VOMICA SEED 30 [hp_C]/1 1
INACTIVE INGREDIENTS: SUCROSE; LACTOSE, UNSPECIFIED FORM

Quit Smoking Symptom Relief Kit

Active ingredients** (in each pellet)

Lobelia inflata 6C HPUS (0.44 mg) (contains less than 10^-12 mg lobeline alkaloids per pellet)

Nux vomica 30C HPUS (0.44 mg) (contains less than 10-^12 mg strychnine alkaloids per pellet)

The letters "HPUS" indicate that the components in this product are officially monographed in the Homeopathic Pharmacopoeia of the United States.

Purpose*

Lobelia inflata 6C HPUS (0.44 mg) ... Relieves nausea associated with nicotine withdrawal

Nux vomica 30C HPUS (0.44 mg) ... Relieves irritability and digestive upset associated with nicotine withdrawal

INDICATIONS AND USAGE

temporarily relieves symptoms associated with nicotine withdrawal such as:

- nausea
- irritability
- digestive upset

Stop use and ask doctor if symptoms for more than 3 days or worsen.

PREGNANCY OR BREAST FEEDING

If pregnant or breastfeeding, ask a health professional before use.

Keep out of reach of children. In case of overdose, get medical help or contact a Poison Control Center right away.

DOSAGE AND ADMINISTRATION

Directions Retain this carton for full directions.

Adults 21 years of age and older:

Nausea: At the onset of symptoms, dissolve 5 pellets of Lobelia inflata 6C under the tongue 3 times a day until symptoms are relieved or as directed by a doctor.

Irritability or Digestive Upset: At the onset of symptoms, dissolve 5 pellets of Nux vomica 30C under the tongue 3 times a day until symptoms are relieved or as directed by a doctor.

INACTIVE INGREDIENT

lactose, sucrose

QUESTIONS

BoironUSA.com

Info@Boiron.com

1-800-BOIRON-1 (1-800-264-7661)

Made in France

Distributed by Boiron, Inc.

Newtown Square, PA 19073

do not use if glued end flaps are open or if pellet dispenser seal is broken

contains 0.25 g of sugar per dose

Turn tube upside down

Twist until 5 pellets are dispensed

Remove cap and pour pellets under the tongue

3 Tubes

Approx. 80 pellets each

Total 240 pellets

Meltaway pellets

Nausea Irritability Digestive Upset*

*CLAIMS BASED ON TRADITIONAL HOMEOPATHIC PRACTICE NOT ACCEPTED MEDICAL EVIDENCE. NOT FDA EVALUATED.
**C,K,CK, and X are homeopathic dilutions: see BoironUSA.com/info for details.